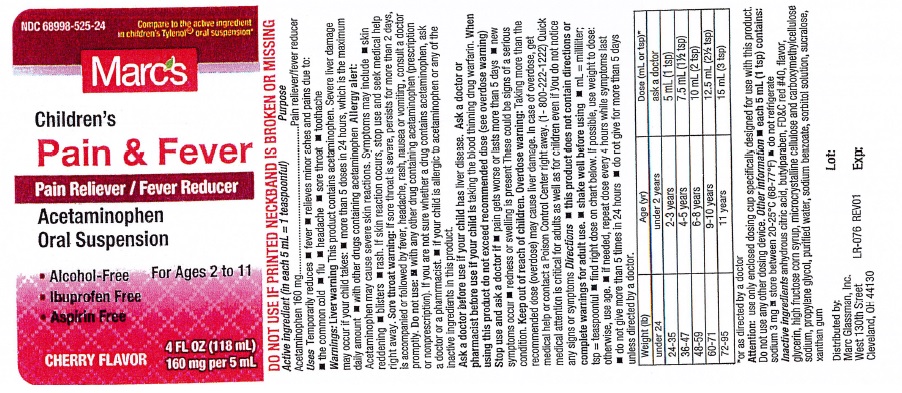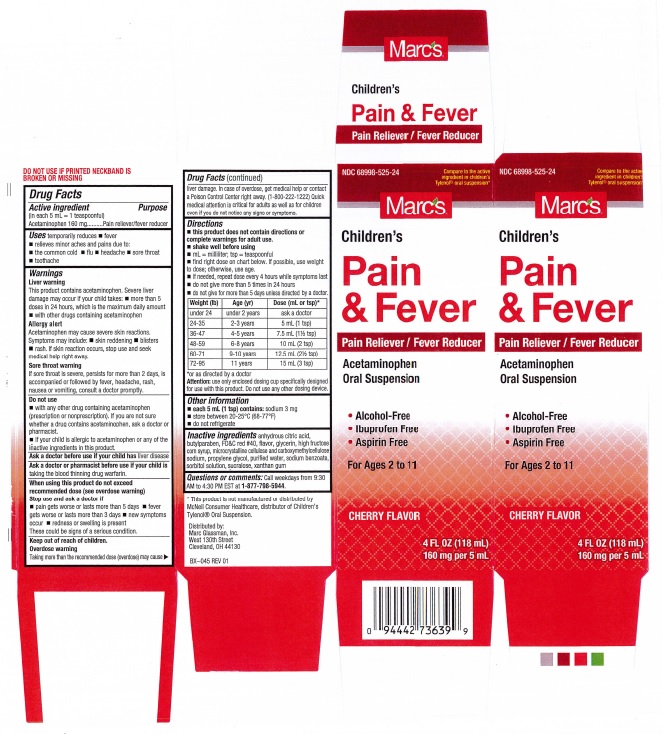 DRUG LABEL: Childrens Pain and Fever
NDC: 68998-525 | Form: LIQUID
Manufacturer: Marc Glassman, Inc.
Category: otc | Type: HUMAN OTC DRUG LABEL
Date: 20251219

ACTIVE INGREDIENTS: ACETAMINOPHEN 160 mg/5 mL
INACTIVE INGREDIENTS: ANHYDROUS CITRIC ACID; BUTYLPARABEN; FD&C RED NO. 40; GLYCERIN; HIGH FRUCTOSE CORN SYRUP; CELLULOSE, MICROCRYSTALLINE; CARBOXYMETHYLCELLULOSE SODIUM; PROPYLENE GLYCOL; WATER; SODIUM BENZOATE; SORBITOL; SUCRALOSE; XANTHAN GUM

Drug Facts Active ingredient

Active ingredient

(in each 5 mL = 1 teaspoonful)

Acetaminophen 160 mg

Purpose

Pain reliver/fever reducer

Keep out of reach of children.

Uses

temporarily reduces

- fever
- relieves minor aches and pains to:
- the common cold
- flu
- headache
- sore throat
- toothache

Warnings

Liver warning
This product contains acetaminophen. Severe liver
damage may occur if your child takes: ■ more than 5
doses in 24 hours, which is the maximum daily amount
■ with other drugs containing acetaminophen

Allergy alert
Acetaminophen may cause severe skin reactions.
Symptoms may include: ■ skin reddening ■ blisters
■ rash. If skin reaction occurs, stop use and seek
medical help right away

Sore throat warning
If sore throat is severe, persists for more than 2 days, is
accompanied or followed by fever, headache, rash,
nausea or vomiting, consult a doctor promptly.

Do not use

- with any other drug containing acetaminophen (prescription or nonprescription). If you are not sure whether a drug contains acetaminophen, ask a doctor or pharmacist.
- if your child is allergic to acetaminophen or any of the inactive ingredients in this product.

Ask a doctor before use if your child has

liver disease

Ask a doctor or pharmacist before use if your child is

taking the blood thinning drug warfarin.

When using this product do not exceed recommended dose (see overdose warning) Stop use and ask a doctor if

- pain gets worse or lasts more than 5 days
- fever gets worse or lasts more than 3 days
- new symptoms occur
- redness or swelling is present

These could be signs of a serious condition.

Overdose warning

Taking more than the recommended dose (overdose) may cause liver damage. In case of overdose, get medical help or contact a Poison Control Center right awway. (1-800-222-1222) Quick medical attention is critical for adults as well as for children even if you do not notice any signs or symptoms.

Directions

- This product does not contain directions or complete warnings for adult use.
- shake well before using
- mL = milliliter; tsp = teaspoonful
- find right dose on chart below. If possible, use weight to dose; otherwise, use age.
- if needed, repeat dose every 4 hours while symptoms last
- do not give more than 5 times in 24 hours
- do not give for more than 5 days unless directed by a doctor

Weight (lb) | Age (yr) | Dose (mL or tsp)*
under 24 | under 2 years | ask a doctor
24-35 | 2-3 years | 5 mL (1 tsp)
36-47 | 4-5 years | 7.5 mL (1 1/2 tsp)
48-59 | 6-8 years | 10 mL (2 tsp)
60-71 | 9-10 years | 12.5 mL (2 1/2 tsp)
72-95 | 11 years | 15 mL (3 tsp)

* or use as directed

Attention:use only enclosed dosing cup specifically designed for use with this product. Do not use any other dosing device.

Other information

- each 5 mL (1 tsp) contains: sodium 3 mg
- store between 20-25°C (68-77°F)
- do not refrigerate

Inactive ingredients

anhydrous citric acid, butylparaben, FD and C red # 40, flavor, glycerin, high fructose corn syrup, microcrystalline cellulose and carboxymethylcellulose sodium, propylene glycol, purified water, sodium benzoate, sorbitol solution, sucralose, xanthan gum

Marcs Childrens Pain and Fever Product Label

NDC 68998-525-24

Compare to the active ingredient in childrens Tylenol® oral suspension*

MARCS

Childrens

Pain and Fever

Pain Reliver / Fever Reducer

Acetaminophen Oral Suspension

- Alcohol-Free
- Ibuprofen Free
- Asprin Free

For Ages 2 to 11

CHERRY FLAVOR

4 FL OZ (118 mL)

160 mg per 5 mL

DO NOT USE IF PRINTED NECKBAND IS BROKEN OR MISSING

* This product is not manufactured or distributed by McNeil Consumer Healthcare, Distributer of Childrens Tylenol® Oral Suspension

Distributed by:

Marc Glassman, Inc.

West 130th Street

Cleveland, OH 44130

BX-045

LR-076

Lot:

Exp:

rres